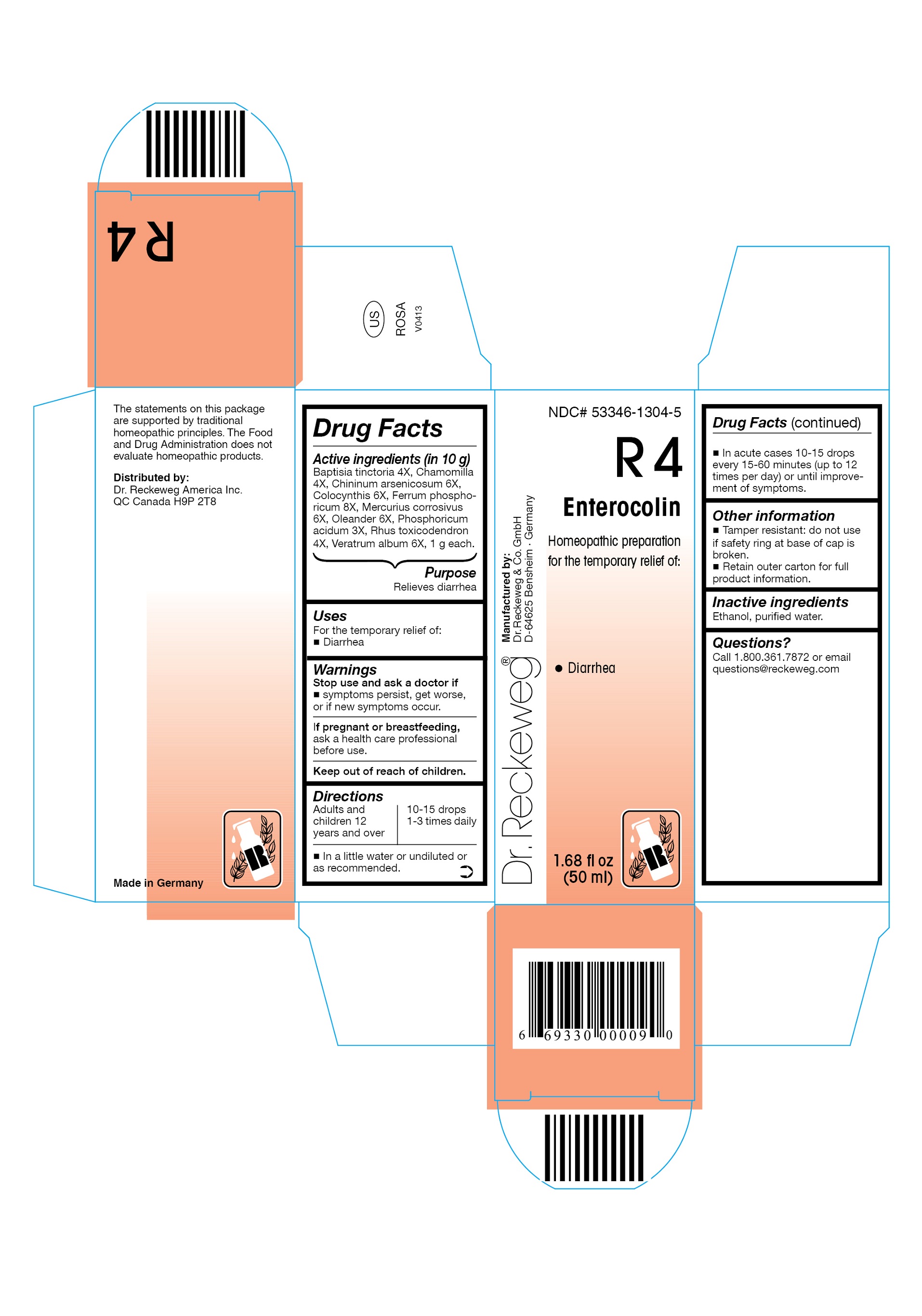 DRUG LABEL: DR. RECKEWEG R4 Enterocolin
NDC: 53346-1304 | Form: LIQUID
Manufacturer: PHARMAZEUTISCHE FABRIK DR. RECKEWEG & CO
Category: homeopathic | Type: HUMAN OTC DRUG LABEL
Date: 20130402

ACTIVE INGREDIENTS: BAPTISIA TINCTORIA ROOT 4 [hp_X]/50 mL; MATRICARIA RECUTITA 4 [hp_X]/50 mL; QUININE ARSENITE 6 [hp_X]/50 mL; CITRULLUS COLOCYNTHIS FRUIT PULP 6 [hp_X]/50 mL; FERRIC PHOSPHATE 8 [hp_X]/50 mL; MERCURIC CHLORIDE 6 [hp_X]/50 mL; NERIUM OLEANDER LEAF 6 [hp_X]/50 mL; PHOSPHORIC ACID 3 [hp_X]/50 mL; TOXICODENDRON PUBESCENS LEAF 4 [hp_X]/50 mL; VERATRUM ALBUM ROOT 6 [hp_X]/50 mL
INACTIVE INGREDIENTS: ALCOHOL; WATER 

DR. RECKEWEG R4 Enterocolin

Active ingredients:
Baptisia tinctoria 4X, Chamomilla 4X, Chininum arsenicosum 6X, Colocynthis 6X, Ferrum phosphoricum 8X, Mercurius corrosivus 6X, Oleander 6X, Phosphoricum acidum 3X, Rhus toxicodendron 4X, Veratrum album 6X, 1 g each in 10 g.

Purpose

Relieves diarrhea

Uses

For the temporary relief of:

- Diarrhea

Warnings

Stop use and ask a doctor if symptoms persist, get worse, or if new symptoms occur.

PREGNANCY OR BREAST FEEDING

If pregnant or breastfeeding, ask a health care professional before use.

Keep out of reach of children.

Directions
Adults and children ≥ 12 years 10-15 drops 1-3 times daily;

acute cases 10-15 drops every 15-60 minutes (up to 12 times per day) or until improvement of symptoms, in a little water or undiluted or as recommended.

Other information

- Tamper resistant: do not use if safety ring at base of cap is broken.
- Retain outer carton for full product information.

Inactive ingredients

Ethanol, purified water.

Questions?

Call 1-800-361-7872 or email questions@reckeweg.com

PACKAGE LABEL

NDC# 53346-1304-5

Dr. Reckeweg R4 Enterocolin

Homeopathic preparation for the temporary relief of:

- Diarrhea

Manufactured by:

Dr. Reckeweg Co. GmbH

D-64625 Bensheim

Germany

1.68 fl oz
(50 ml